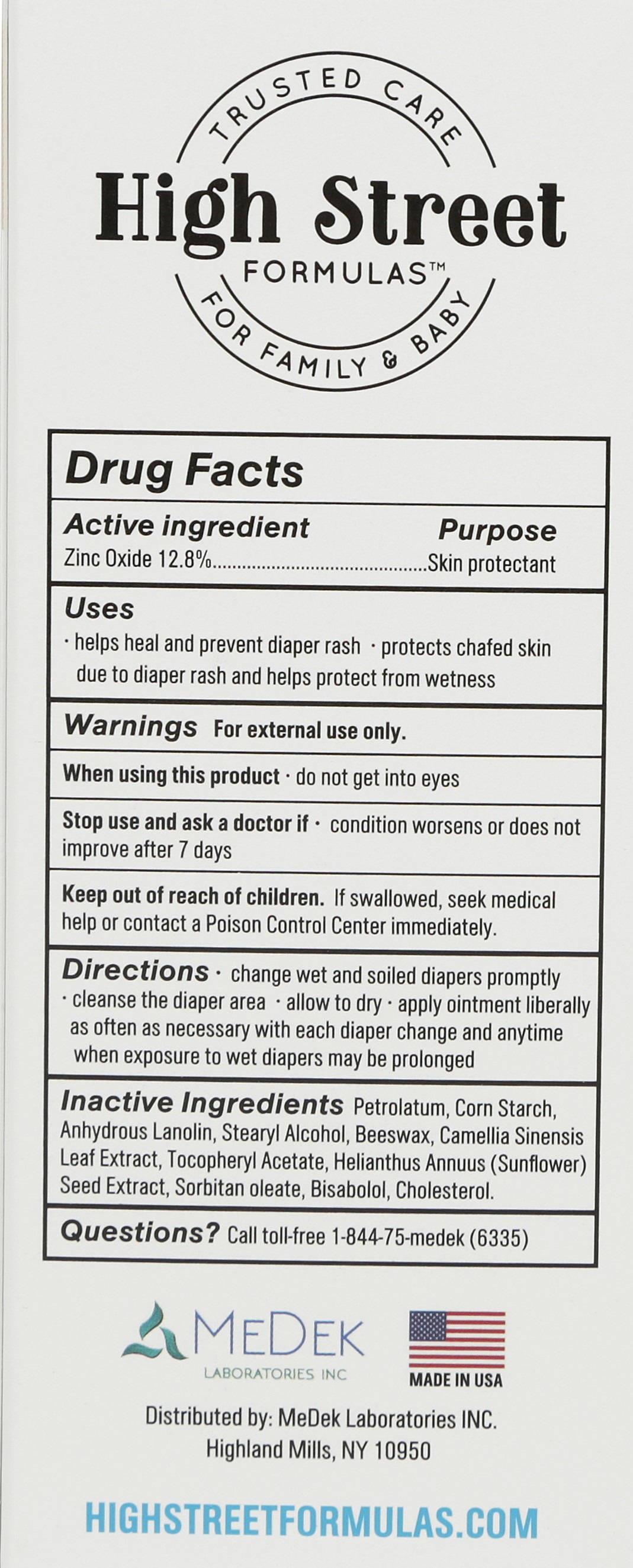 DRUG LABEL: diaper
NDC: 71969-111 | Form: OINTMENT
Manufacturer: Medek Laboratories Inc.
Category: otc | Type: HUMAN OTC DRUG LABEL
Date: 20191203

ACTIVE INGREDIENTS: ZINC OXIDE 21.76 g/100 g
INACTIVE INGREDIENTS: PETROLATUM; STARCH, CORN; LANOLIN; STEARYL ALCOHOL; CANDELILLA WAX; CAMELLIA SINENSIS FLOWER; TOCOL ACETATE; HELIANTHUS ANNUUS SEED WAX; PEG-6 SORBITAN OLEATE; BISABOLOL OXIDE A; CHOLESTEROL

Drug Facts

Active Ingredients Purpose

Zinc Oxide 12.8%..............................................................Skin Protectant

Purpose

Skin Protectant

Warnings

FOR EXTERNAL USE ONLY

When using this product keep out of eyes.

Stop use and ask a doctor if condition worsens or does not improve after 7 days

Keep out of reach of children

Other Information

protect this product from excessive heat and direct sun

Inactive Ingredients

Petrolatum, corn starch, anhydrous lanolin, stearyl alcohol, beeswax, camellia sinensis leaf extract, tocopheryl acetate, sunflower seed extract, sorbitan oleate, bisabolol, cholesterol

Indications

Uses

Help heal and prevent diaper rash

Protects chafed skin due to diaper rash and helps protect wetness

Do Not Use

Discontinue use if irritation occurs.

Ask a doctor if condition worsens

Directions

change wet and soiled diapers promptly

cleanse the diaper area

allow to dry

apply ointment liberally as often as necessary with each diaper change and anytime when exposure to wet diapers may be prolonged

dosage

apply ointment liberally as often as necessary with each diaper change and anytime when exposure to wet diapers may be prolonged